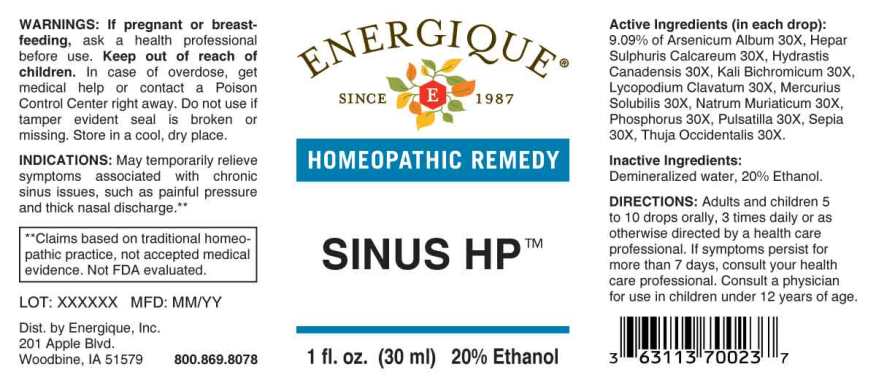 DRUG LABEL: Sinus HP
NDC: 44911-0629 | Form: LIQUID
Manufacturer: Energique, Inc.
Category: otc | Type: HUMAN OTC DRUG LABEL
Date: 20231219

ACTIVE INGREDIENTS: ARSENIC TRIOXIDE 30 [hp_X]/1 mL; CALCIUM SULFIDE 30 [hp_X]/1 mL; GOLDENSEAL 30 [hp_X]/1 mL; POTASSIUM DICHROMATE 30 [hp_X]/1 mL; LYCOPODIUM CLAVATUM SPORE 30 [hp_X]/1 mL; MERCURIUS SOLUBILIS 30 [hp_X]/1 mL; SODIUM CHLORIDE 30 [hp_X]/1 mL; PHOSPHORUS 30 [hp_X]/1 mL; PULSATILLA PRATENSIS WHOLE 30 [hp_X]/1 mL; SEPIA OFFICINALIS JUICE 30 [hp_X]/1 mL; THUJA OCCIDENTALIS LEAFY TWIG 30 [hp_X]/1 mL
INACTIVE INGREDIENTS: WATER; ALCOHOL

DRUG FACTS:

ACTIVE INGREDIENTS:

(in each drop): 9.09% of Arsenicum Album 30X, Hepar Sulphuris Calcareum 30X, Hydrastis Canadensis 30X, Kali Bichromicum 30X, Lycopodium Clavatum, Mercurius Solubilis 30X, Natrum Muriaticum 30X, Phosphorus 30X, Pulsatilla (Pratensis) 30X, Sepia 30X, Thuja Occidentalis 30X.

INDICATIONS:

May temporarily relieve symptoms associated with chronic sinus issues, such as painful pressure and thick nasal discharge.**

**Claims based on traditional homeopathic practice, not accepted medical evidence. Not FDA evaluated.

WARNINGS:

If pregnant or breast-feeding, ask a health professional before use.

Keep out of reach of children. In case of overdose, get medical help or contact a Poison Control Center right away.

Do not use if tamper evident seal is broken or missing. Store in a cool, dry place.

KEEP OUT OF REACH OF CHILDREN.

In case of overdose, get medical help or contact a Poison Control Center right away.

DIRECTIONS:

Adults and children 5 to 10 drops orally, 3 times daily or as otherwise directed by a health care professional. If symptoms persist for more than 7 days, consult your health care professional. Consult a physician for use in children under 12 years of age.

INDICATIONS:

May temporarily relieve symptoms associated with chronic sinus issues such as painful pressure and thick nasal discharge.**

**Claims based on traditional homeopathic practice, not accepted medical evidence. Not FDA evaluated.

INACTIVE INGREDIENTS:

Demineralized water, 20% Ethanol.

QUESTIONS:

Dist. by Energique, Inc.

201 Apple Blvd

Woodbine, IA 51579 800-869-8078

PACKAGE LABEL DISPLAY:

ENERGIQUE

since 1987

HOMEOPATHIC REMEDY

SINUS HP

1 fl. oz. (30 ml)